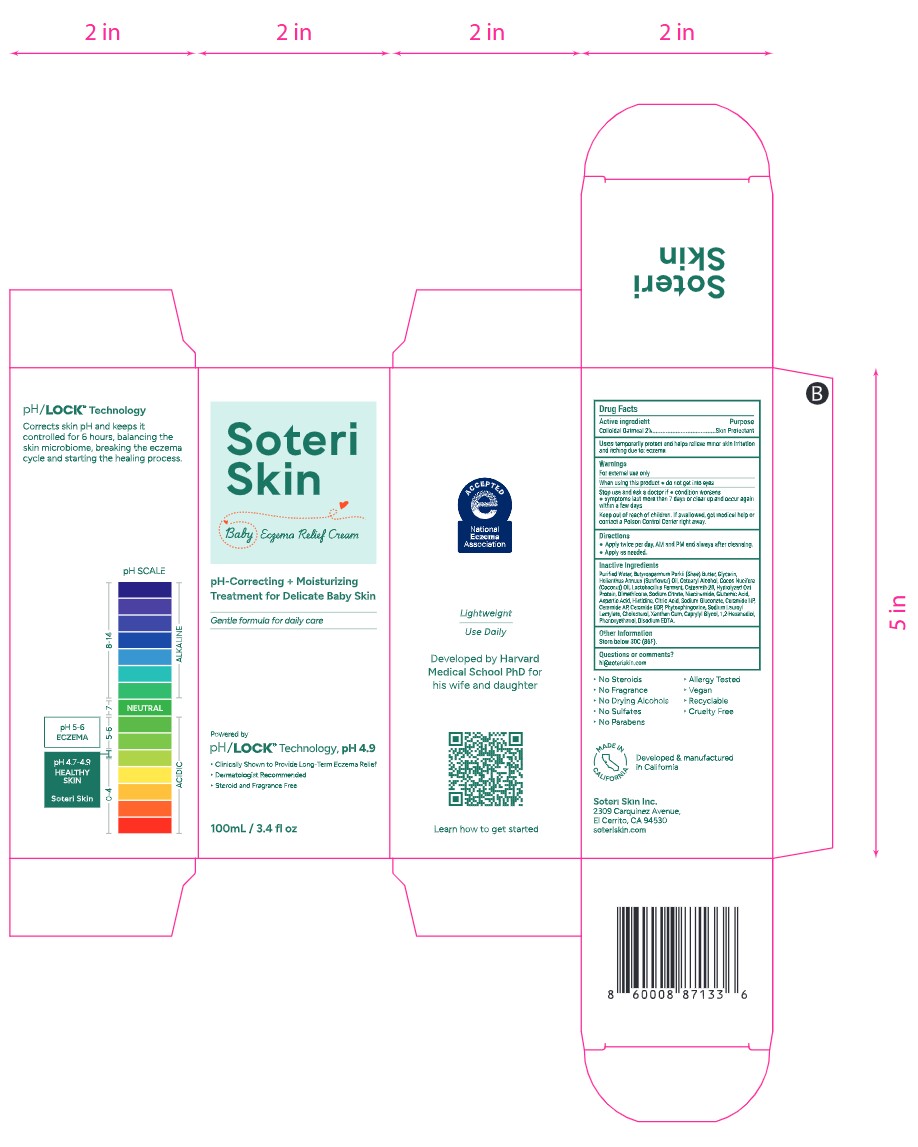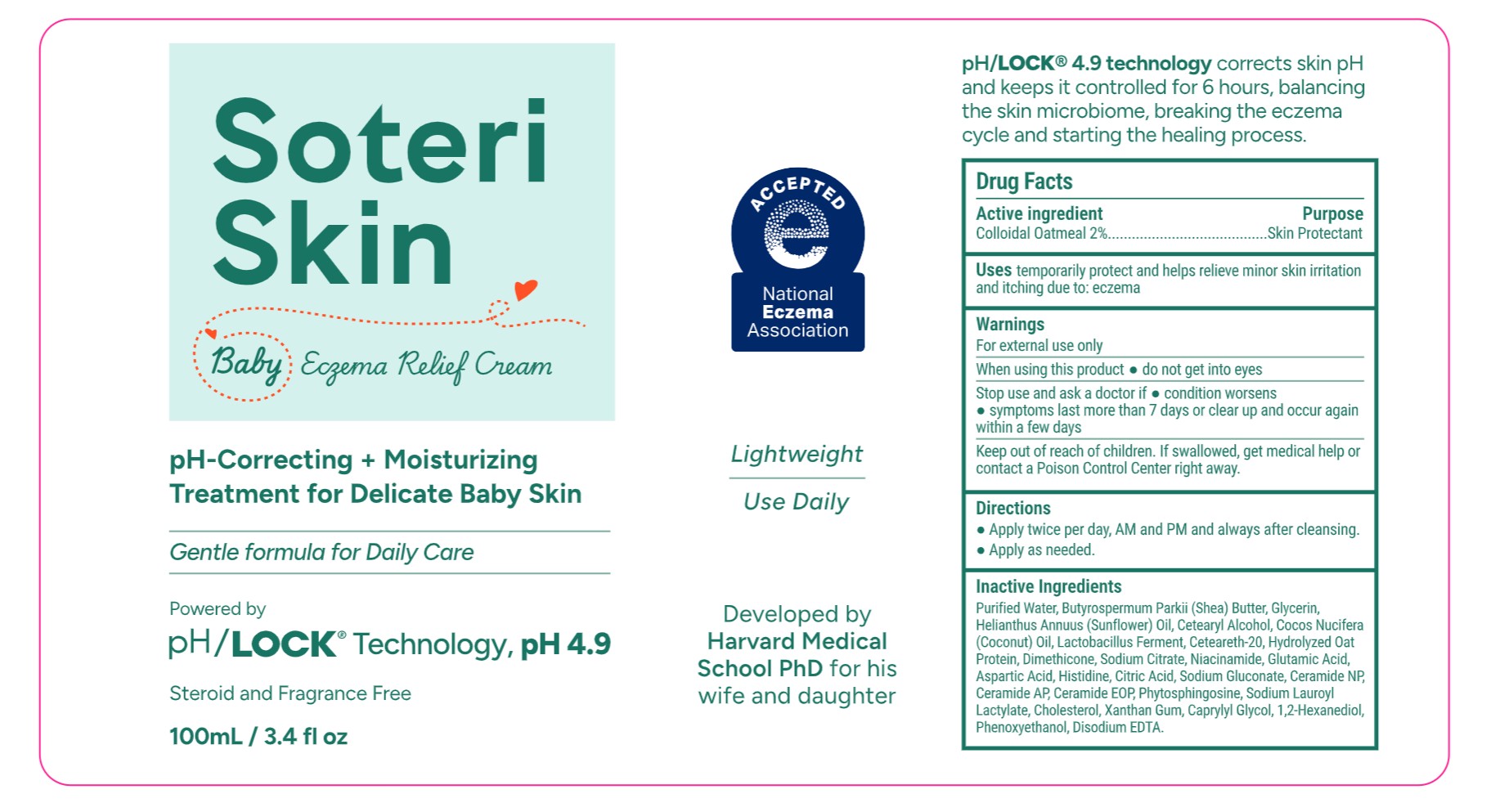 DRUG LABEL: Soteri Skin Baby Eczema Relief Cream
NDC: 85265-104 | Form: EMULSION
Manufacturer: Soteri Skin, Inc
Category: otc | Type: HUMAN OTC DRUG LABEL
Date: 20251210

ACTIVE INGREDIENTS: OATMEAL 2 g/100 mL
INACTIVE INGREDIENTS: CHOLESTEROL; 1,2-HEXANEDIOL; DIMETHICONE; SODIUM GLUCONATE; OAT; GLUTAMIC ACID; SODIUM LAUROYL LACTYLATE; LACTOBACILLUS; GLYCERIN; NIACINAMIDE; HISTIDINE; XANTHAN GUM; EDETATE DISODIUM; CETEARYL ALCOHOL; CETEARETH-20; ANHYDROUS CITRIC ACID; CAPRYLYL GLYCOL; ASPARTIC ACID; CERAMIDE NP; WATER; PHENOXYETHANOL; CERAMIDE 1; CERAMIDE AP; BUTYROSPERMUM PARKII (SHEA) BUTTER; HELIANTHUS ANNUUS (SUNFLOWER) SEED OIL; SODIUM CITRATE

Soteri Skin Baby Eczema Relief Cream NDC 85265-104

Active Ingredient

Colloidal Oatmeal 2%

Uses

temporarily protect and helps relieve minor skin irritation and itching due to: eczema

Purpose

Skin Protectant

Warnings

For external use only

When using this product

- do not get into eyes

Stop use and ask a doctor if

- condition worsens
- symptoms last more than 7 days or clear up and occur again within a few days

Keep out of reach of children

If swallowed, get medical help or contact a Poison Control Center right away.

Directions

- Apply twice per day, AM and PM and always after cleansing.
- Apply as needed.

Inactive Ingredients

Purified Water, Butyrospermum Parkii (Shea) Butter, Glycerin, Helianthus Annuus (Sunflower) Oil, Cetearyl Alcohol, Cocos Nucifera
(Coconut) Oil, Lactobacillus Ferment, Ceteareth-20, Hydrolyzed Oat Protein, Dimethicone, Sodium Citrate, Niacinamide, Glutamic Acid, Aspartic Acid, Histidine, Citric Acid, Sodium Gluconate, Ceramide NP, Ceramide AP, Ceramide EOP, Phytosphingosine, Sodium Lauroyl Lactylate, Cholesterol, Xanthan Gum, Caprylyl Glycol, 1,2-Hexanediol, Phenoxyethanol, Disodium EDTA.